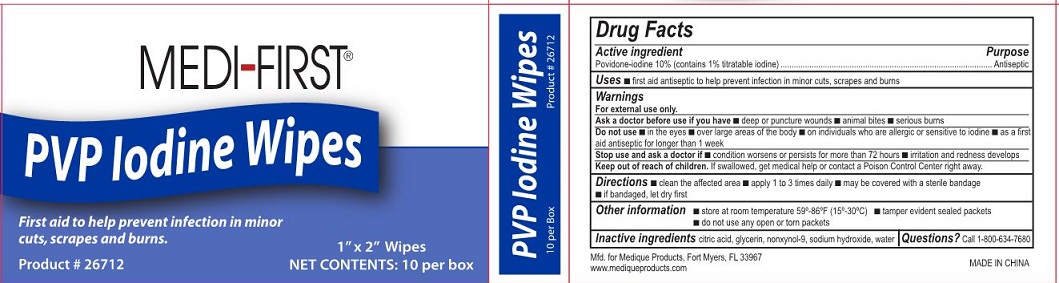 DRUG LABEL: Medi-First PVP Iodine Wipes
NDC: 47682-267 | Form: SWAB
Manufacturer: Unifirst-First Aid
Category: otc | Type: HUMAN OTC DRUG LABEL
Date: 20250908

ACTIVE INGREDIENTS: POVIDONE-IODINE 10 mg/1 mL
INACTIVE INGREDIENTS: CITRIC ACID MONOHYDRATE; GLYCERIN; WATER; NONOXYNOL-9; SODIUM HYDROXIDE

Medi-First PVP Iodine Wipes

Active ingredient

Povidone-iodine 10%

(contains 1% titratable iodine)

Purpose

Antiseptic

Uses

- first aid antiseptic to help prevent infection in minor cuts, scrapes and burns

Warnings

For external use only.

Ask a doctor before use if you have

- deep or puncture wounds
- animal bites
- serious burns

Do not use

- in the eyes
- over large areas of the body
- on individuals who are allergic or sensative to iodine
- as a first aid atiseptic for longer than 1 week

Stop use and ask a doctor if

- condition worsens or persists for more than 72 hours
- irritation and redness develops

Keep out of reach of children.

If swallowed, get medical help or contact a Poison Control Center right away.

Directions

- clean the affected area
- apply1 to 3 times daily
- may be covered with a sterile bandage
- if bandaged, let dry first

Other information

- store at controlled temperature 59-86ºF (15-30ºC)

Inactive ingredients

citric acid, glycerin, nonxynol-9, sodium hydroxide, water

Questions?

Call 1-800-634-7680

Medi-First PVP Iodine Label

Medi-First®

PVP Iodine Wipes

Product # 26712

1" x 2" Wipes

Net Contents: 10 per box